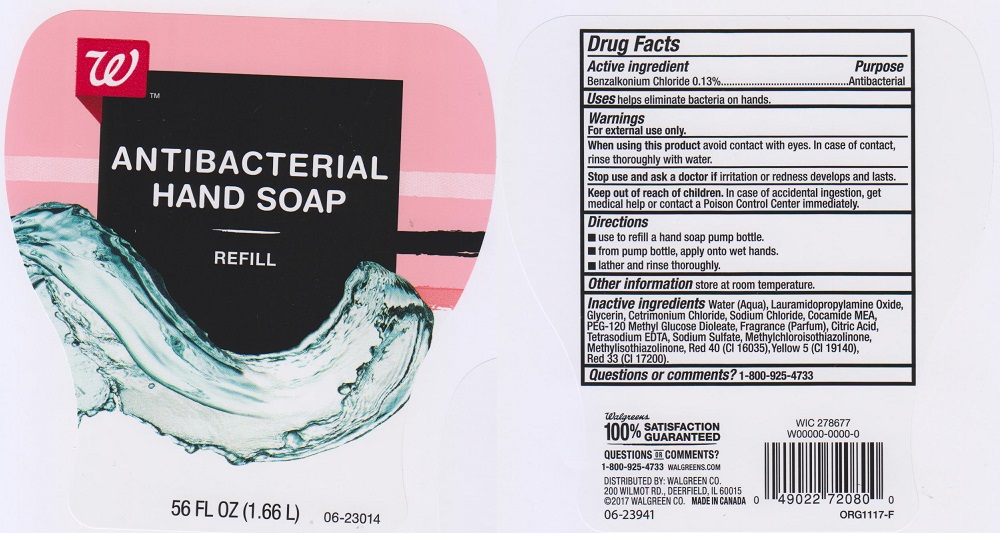 DRUG LABEL: Walgreens

NDC: 0363-7211 | Form: LIQUID
Manufacturer: WALGREEN COMPANY
Category: otc | Type: HUMAN OTC DRUG LABEL
Date: 20220912

ACTIVE INGREDIENTS: BENZALKONIUM CHLORIDE 1.3 mg/1 mL
INACTIVE INGREDIENTS: WATER; CETRIMONIUM CHLORIDE; GLYCERIN; LAURAMIDOPROPYLAMINE OXIDE; COCO MONOETHANOLAMIDE; SODIUM CHLORIDE; PEG-120 METHYL GLUCOSE DIOLEATE; CITRIC ACID MONOHYDRATE; EDETATE SODIUM; SODIUM SULFATE; METHYLCHLOROISOTHIAZOLINONE; METHYLISOTHIAZOLINONE; FD&C RED NO. 40; FD&C YELLOW NO. 5; D&C RED NO. 33

0363-7211, Walgreens

Active ingredient

Benzalkonium Chloride 0.13%

Purpose

Antibacterial

Uses

Helps eliminate bacteria on hands

Warnings

For external use only.

When using this product

avoid contact with eyes. In case of contact, rinse thoroughly with water.

Stop use and ask doctor if

irritation or redness develops and lasts.

Keep out of reach of children.

In case of accidental ingestion, get medical help or contact a Poison Control Center immediately.

Directions

- use to refill a hand soap pump bottle
- from pump bottle, apply onto wet hands
- lather and rinse thoroughly

Other informaton

store at room temperature

Inactive ingredients

Water (Aqua), Lauramidopropylamine Oxide, Glycerin, Cetrimonium Chloride, Sodium Chloride, Cocamide MEA, PEG-120 Methyl Glucose Dioleate, Fragrance (Parfum), Citric Acid, Tetrasodium EDTA, Sodium Sulfate, Methylchloroisothiazolinone, Methylisothiazolinone, Red 40 (CI 16035), Yellow 5 (CI 19140), Red 33 (CI 17200)

Questions or comments?

1-800-925-4733